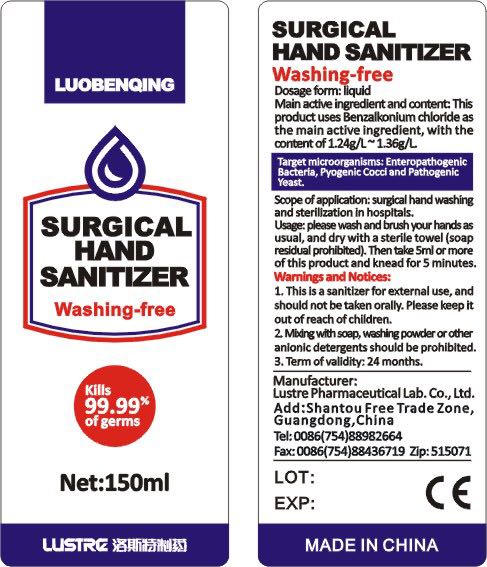 DRUG LABEL: luobenqing Surgical hand sanitizer
NDC: 53042-001 | Form: LIQUID
Manufacturer: LUSTRE Pharmaceutical Lab.Co.,Ltd.
Category: otc | Type: HUMAN OTC DRUG LABEL
Date: 20200408

ACTIVE INGREDIENTS: BENZALKONIUM CHLORIDE 0.195 mg/150 mL
INACTIVE INGREDIENTS: WATER

INDICATIONS AND USAGE

please washandbrushyour hands as usual, and dry with a sterile towel (soapresidual prohibited).

Then take 5ml or more of this product and knead for 5 minutes.

DOSAGE AND ADMINISTRATION

surgical hand washing and sterilization in hospltals.

INACTIVE INGREDIENT

water

ACTIVE INGREDIENT

Benzalkonium chloride

PURPOSE

Disinfection
Sterilization
No Rinseing

WARNINGS

This is a sanitizer for external use, and should not be taken orally.

Please keep it out of reach of children.
Miding wilth soap, washing powder or other anlonic detergents should be prohiblited.
Term ofvalidity: 24 months.

keep out of reach of children